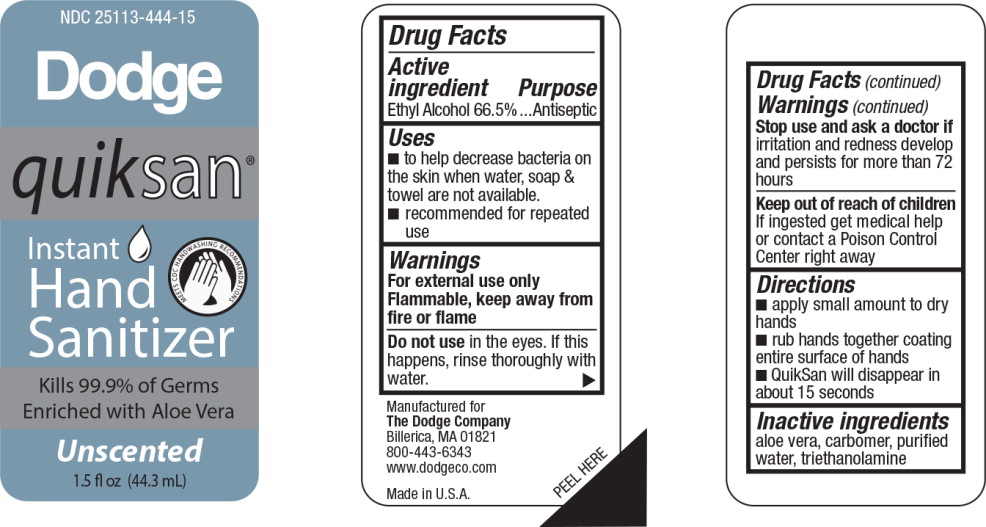 DRUG LABEL: Instant Hand Sanitizer
NDC: 25113-444 | Form: GEL
Manufacturer: Dodge
Category: otc | Type: HUMAN OTC DRUG LABEL
Date: 20150210

ACTIVE INGREDIENTS: alcohol 665 mg/1 L
INACTIVE INGREDIENTS: aloe; water; trolamine

Drug Facts

Active ingredient

Ethyl Alcohol 66.5%

Purpose

Antiseptic

Uses

- to help decrease bacteria on the skin when water, soap & towel are not available.
- recommended for repeated use

Warnings

For external use only

Flammable, keep away from fire or flame

Do not use in the eyes. If this happens, rinse thoroughly with water.

Stop use and ask a doctor if irritation and redness develop and persists for more than 72 hours

Keep out of reach of children

If ingested get medical help or contact a Poison Control Center right away

Directions

- apply small amount to dry hands
- rub hands together coating entire surface of hands
- QuikSan will disappear in about 15 seconds

Inactive ingredients

aloe vera, carbomer, purified water, triethanolamine

Principal Display Panel - 1.5 fl oz Bottle Label

NDC 25113-444-15

quiksan®

Instant Hand Sanitizer

MEETS CDC HANDWASHING RECOMMENDATIONS

Kills 99.9% of Germs

Enriched with Aloe Vera

Unscented

1.5 fl oz (44.3 mL)